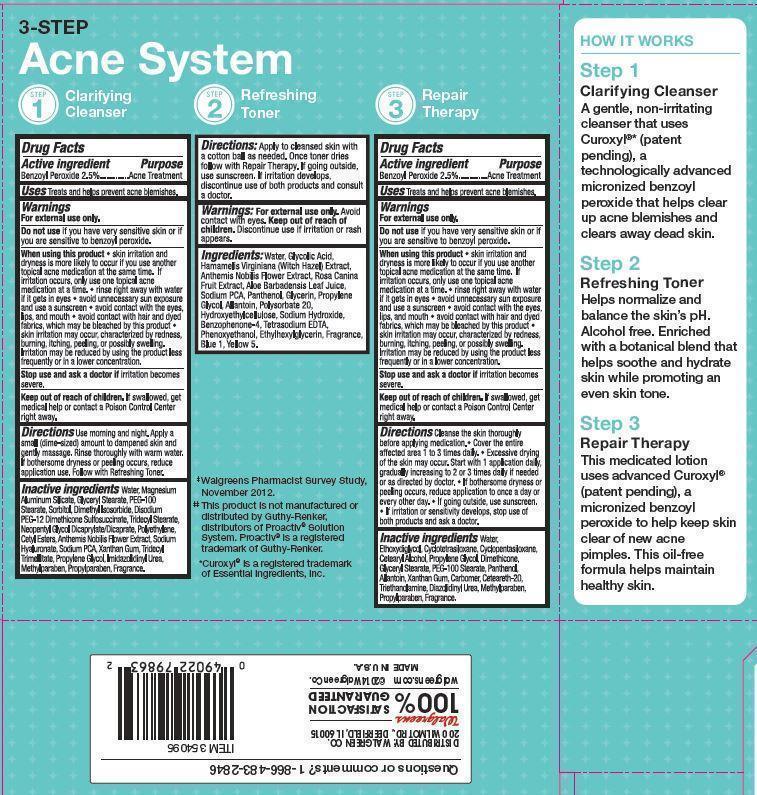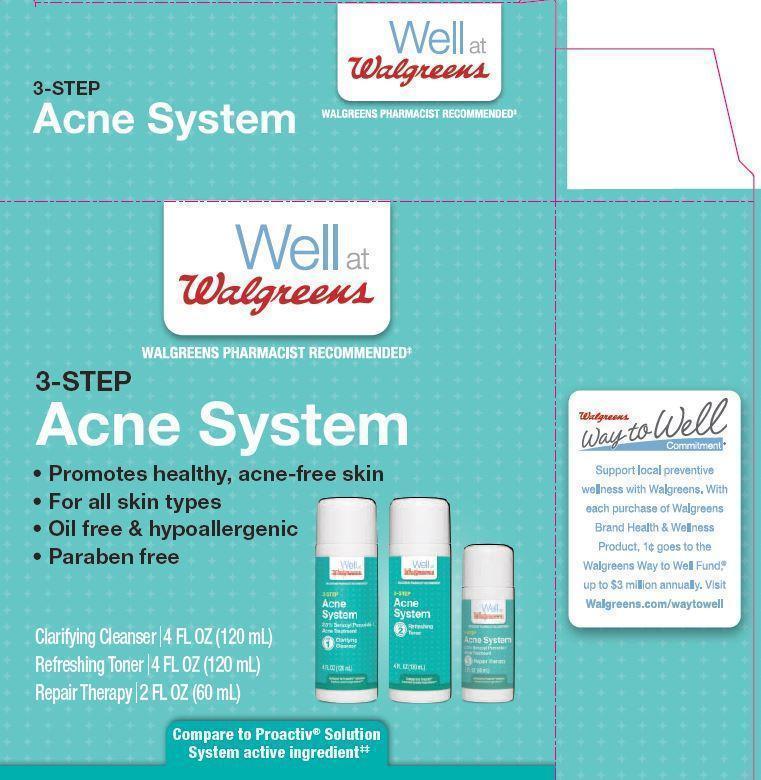 DRUG LABEL: 3 Step Acne System
NDC: 0363-3226 | Form: KIT | Route: TOPICAL
Manufacturer: Walgreens
Category: otc | Type: HUMAN OTC DRUG LABEL
Date: 20180222

ACTIVE INGREDIENTS: Benzoyl Peroxide 2.5 g/100 mL; Benzoyl Peroxide 2.5 g/100 mL
INACTIVE INGREDIENTS: Water; Magnesium Aluminum Silicate; GLYCERYL MONOSTEARATE; PEG-100 Stearate; Sorbitol; Dimethyl Isosorbide; Tridecyl Stearate; Neopentyl Glycol Dicaprylate/Dicaprate; HIGH DENSITY POLYETHYLENE; CETYL ESTERS WAX; CHAMAEMELUM NOBILE FLOWER; HYALURONATE SODIUM; SODIUM PYRROLIDONE CARBOXYLATE; Xanthan Gum; Tridecyl Trimellitate; Propylene Glycol; IMIDUREA; Methylparaben; Propylparaben; Water; DIETHYLENE GLYCOL MONOETHYL ETHER; CYCLOMETHICONE 4; CYCLOMETHICONE 5; CETOSTEARYL ALCOHOL; Propylene Glycol; Dimethicone; GLYCERYL MONOSTEARATE; PEG-100 Stearate; Panthenol; Allantoin; Xanthan Gum; POLYOXYL 20 CETOSTEARYL ETHER; TROLAMINE; Diazolidinyl Urea; Methylparaben; Propylparaben

Drug Facts

Active ingredient Purpose

Benzoyl Peroxide - 2.50% Acne Treatment

Uses

• Treats and helps prevent acne blemishes.

Warnings
For external use only.

Do not use if you have very sensitive skin or if you are sensitive to benzoyl peroxide.

When using this product

• skin irritation and dryness is more likely to occur if you use another topical acne medication at the same time. If irritation occurs, only use one topical acne medication at a time. • rinse right away with water if it gets in eyes • avoid unnecessary sun exposure and use a sunscreen •avoid contact with eyes, lips, and mouth • avoid contact with hair and dyed fabrics, which may be bleached by this product • skin irritation may occurs, characterized by redness, burning, itching, peeling, or possibly swelling. Irritation may be reduced by using the product less frequently or in a lower concentration.

Stop use and ask a doctor if irritation becomes severe.

Keep out of reach of the children

If product is swallowed, get medical help or contact a Poison Control Center right away

Directions

Use morning and night. Apply a small (dime-sized) amount to dampened skin and gently massage. Rinse thoroughly with warm water. If bothersome dryness or peeling occurs, reduce application use. Follow with Refreshing Toner.

Inactive ingredients

Water, Magnesium Aluminum Silicate, Glyceryl Stearate, PEG-100 Stearate, Sorbitol, Dimethyl Isosorbide, Disodium PEG-12 Dimethicone Sulfosuccinate, Tridecyl Stearate, Neopentyl Glycol Dicaprylate/Dicaprate, Polyethylene, Cetyl Esters, Anthemis Nobilis Flower Extract,
Sodium Hyaluronate, Sodium PCA, Xanthan Gum, Tridecyl Trimellitate, Propylene Glycol, Imidazolidinyl Urea, Methylparaben, Propylparaben,
Fragrance

Active ingredient Purpose

Benzoyl Peroxide - 2.50% Acne Treatment

Uses

• Treats and helps prevent acne blemishes.

Warnings For external use only.

Do not use if you have very sensitive skin or if you are sensitive to benzoyl peroxide.

When using this product

• skin irritation and dryness is more likely to occur if you use another topical acne medication at the same time. If irritation occurs, only use one topical acne medication at a time. • rinse right away with water if it gets in eyes • avoid unnecessary sun exposure and use a sunscreen •avoid contact with eyes, lips, and mouth • avoid contact with hair and dyed fabrics, which may be bleached by this product • skin irritation may occurs, characterized by redness, burning, itching, peeling, or possibly swelling. Irritation may be reduced by using the product less frequently or in a lower concentration.

Stop use and ask a doctor if irritation becomes severe.

Keep out of reach of the children

If product is swallowed, get medical help or contact a Poison Control Center right away

Directions

• Cleans the skin thoroughly before applying medication • Cover the entire affected area one to three times a day • Excessive drying of the skin may occur. Start with one application daily, then gradually increase to two or three times daily if needed or as directed by a doctor. If bothersome dryness or peeling occurs, reduce application to once a day or every other day. • If going outside, use a sunscreen. If sensitivity develops, discontinue use of both products and consult a doctor.

Inactive ingredients

Water, Ethoxydiglycol, Cyclotetrasiloxane, Cyclopentasiloxane, Cetearyl Alcohol, Propylene Glycol, Dimethicone, lyceryl Stearate, PEG-100 Stearate, Panthenol, Allantoin, Xanthan Gum, Ceteareth-20, Carbomer, Triethanolamine, Diazolidinyl Urea, Methylparaben, Propylparaben,
Fragrance